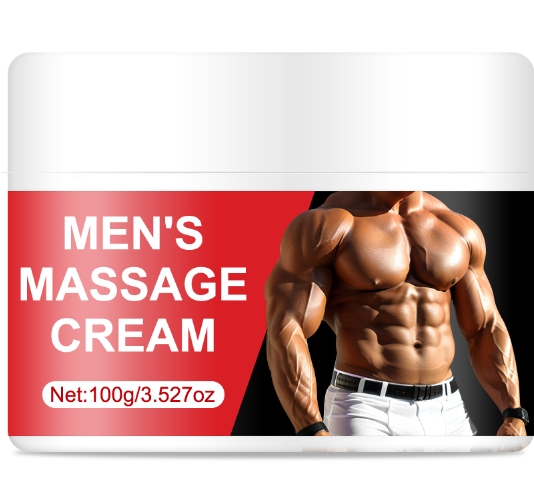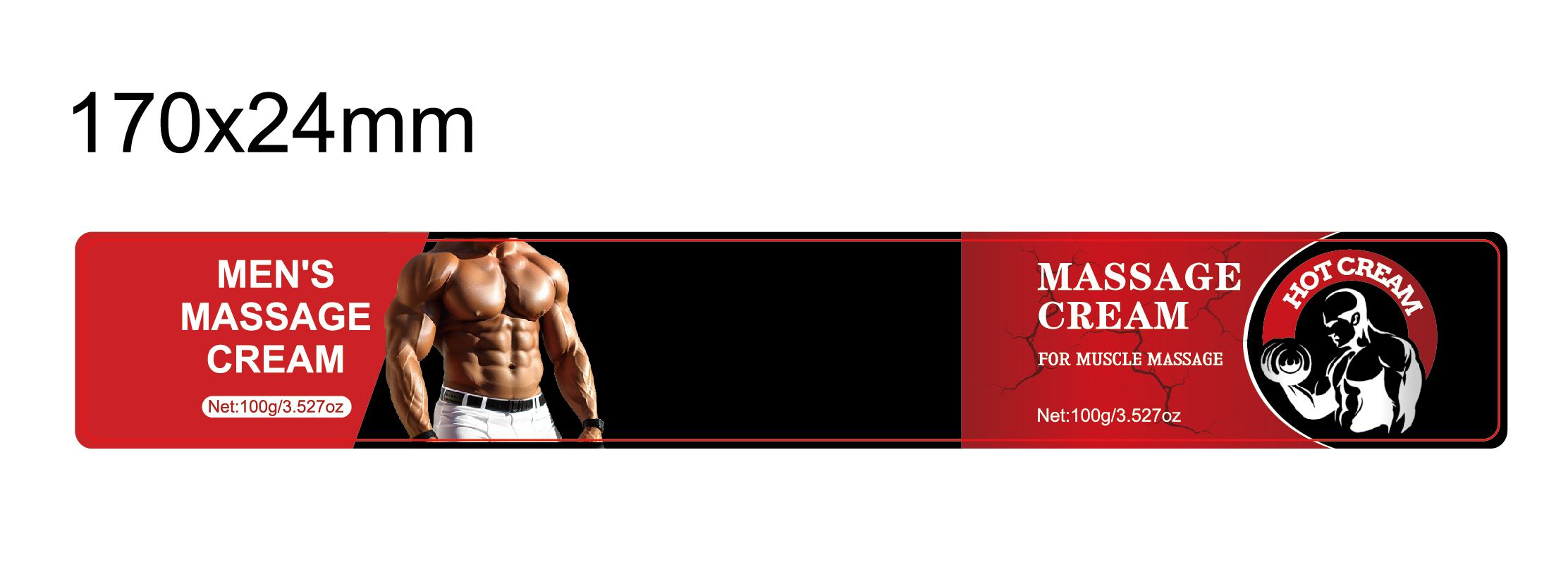 DRUG LABEL: Mens Massage Cream
NDC: 84025-158 | Form: CREAM
Manufacturer: Guangzhou Yanxi Biotechnology Co.. Ltd
Category: otc | Type: HUMAN OTC DRUG LABEL
Date: 20240817

ACTIVE INGREDIENTS: ISOPROPYL MYRISTATE 3 mg/100 g; MINERAL OIL 5 mg/100 g
INACTIVE INGREDIENTS: WATER

DOSAGE AND ADMINISTRATION

Cream for muscle massage

WARNINGS

Keep out of children

INACTIVE INGREDIENT

Aqua

INDICATIONS AND USAGE

For daily men's skin care

Keep out of children

PURPOSE

For men's muscle skin care